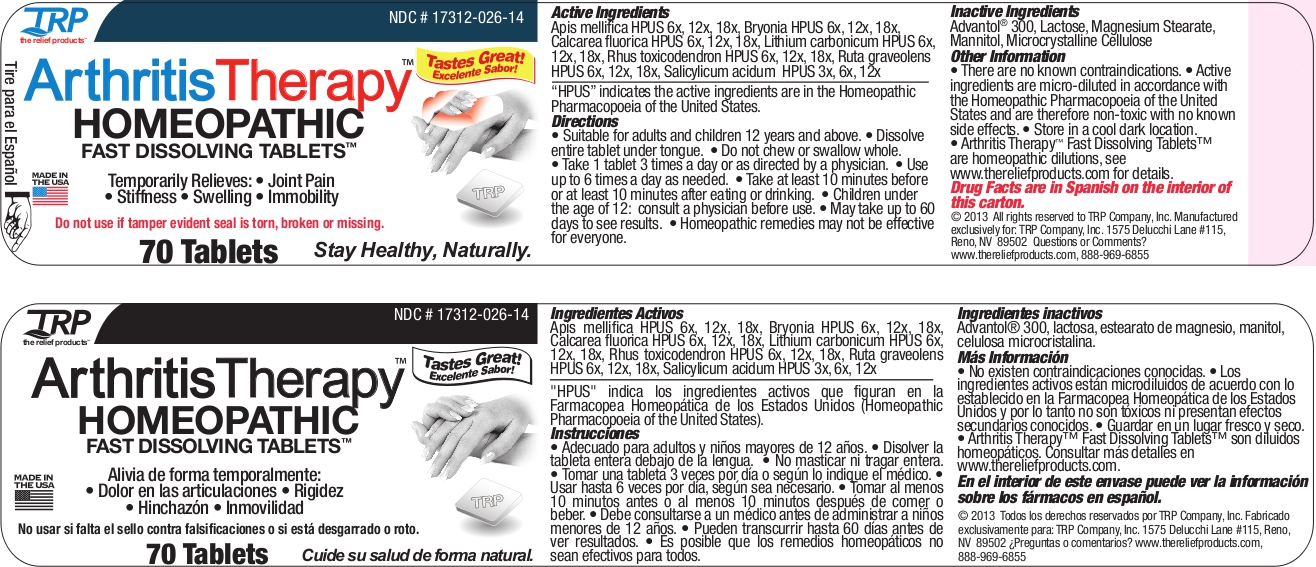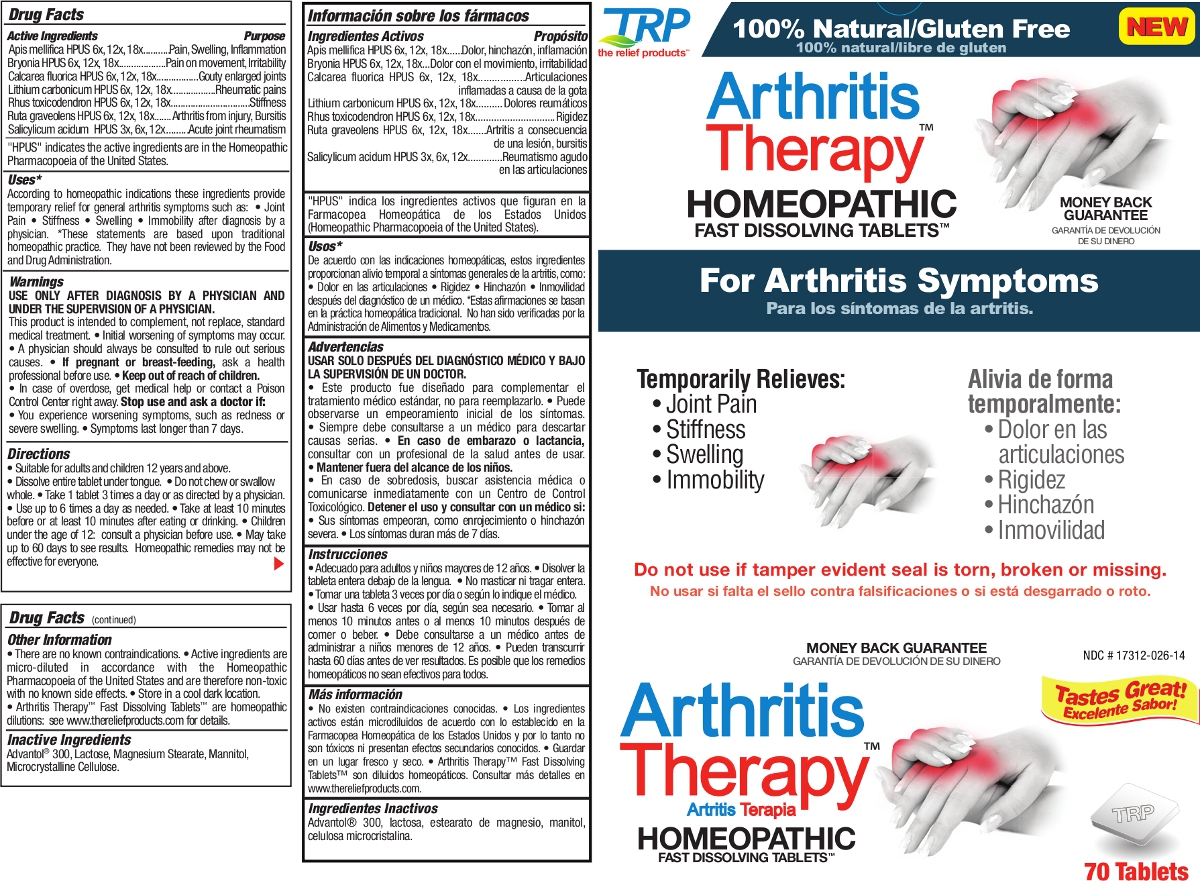 DRUG LABEL: Arthritis Therapy
NDC: 17312-026 | Form: TABLET, ORALLY DISINTEGRATING
Manufacturer: TRP Company
Category: homeopathic | Type: HUMAN OTC DRUG LABEL
Date: 20130905

ACTIVE INGREDIENTS: APIS MELLIFERA 6 [hp_X]/1 1; BRYONIA ALBA ROOT 6 [hp_X]/1 1; CALCIUM FLUORIDE 6 [hp_X]/1 1; LITHIUM CARBONATE 6 [hp_X]/1 1; TOXICODENDRON PUBESCENS LEAF 6 [hp_X]/1 1; RUTA GRAVEOLENS FLOWERING TOP 6 [hp_X]/1 1; SALICYLIC ACID 3 [hp_X]/1 1
INACTIVE INGREDIENTS: MANNITOL; SORBITOL; CROSPOVIDONE; CELLULOSE, MICROCRYSTALLINE; COPOVIDONE; SILICON DIOXIDE; LACTOSE; MAGNESIUM STEARATE

Arthritis Therapy Homeopathic Fast Dissolving Tablets

Active Ingredients |  | Purpose
Apis mellifica HPUS | 6x, 12x, 18x | Pain, Swelling, Inflammation
Bryonia HPUS | 6x, 12x, 18x | Pain on movement, Irritability
Calcarea fluorica HPUS | 6x, 12x, 18x | Gouty enlarged joints
Lithium carbonicum HPUS | 6x, 12x, 18x | Rheumatic pains
Rhus toxicodendron HPUS | 6x, 12x, 18x | Stiffness
Ruta graveolens | 6x, 12x, 18x | Arthritis from injury, Bursitis
Salicylicum acidum | 3x, 6x, 12x | Acute joint rheumatism

"HPUS" indicates the active ingredients are in the Homeopathic Pharmacopoeia of the United States.

Uses

According to homeopathic indications these ingredients provide temporary relief for general arthritis symptoms such as: • Joint Pain • Stiffness • Swelling • Immobility after diagnosis by a physician. *These statements are based upon traditional homeopathic practice. They have not been reviewed by the Food and Drug Administration.

Warnings

USE ONLY AFTER DIAGNOSIS BY A PHYSICIAN AND UNDER THE SUPERVISION OF A PHYSICIAN.

This product is intended to complement, not replace, standard medical treatment.

- Initial worsening of symptoms may occur.
- A physician should always be consulted to rule out serious causes.
- In case of overdose, get medical help or contact a Poison Control Center right away.

Stop use and ask a doctor if:

- You experience worsening symptoms, such as redness or severe swelling.
- If symptoms last longer than 7 days.

PREGNANCY OR BREAST FEEDING

If pregnant or breast-feeding, ask a health professional before use.

Directions

- Suitable for adults and children 12 years and above.
- Dissolve entire tablet under tongue.
- Do not chew or swallow whole.
- Take 1 tablet 3 times a day or as directed by a physician.
- Use up to 6 times a day as needed.
- Take at least 10 minutes before or at least 10 minutes after eating or drinking.
- Children under the age of 12: consult a physician before use.
- May take up to 60 days to see results.
- Homeopathic remedies may not be effective for everyone.

Other information

- There are no known contraindications.
- Active ingredients are micro-diluted in accordance with the Homeopathic Pharmacopoeia of the United States and are therefore non-toxic with no known side effects.
- Store in a cool dark location.
- Arthritis Therapy Fast Dissolving Tablets are homeopathic dilutions, see www.thereliefproducts.com for details.

Inactive Ingredients

Advantol® 300, Lactose, Magnesium Stearate, Mannitol, Microcrystalline Cellulose.

Questions or comments? www.thereliefproducts.com, 888-969-6855